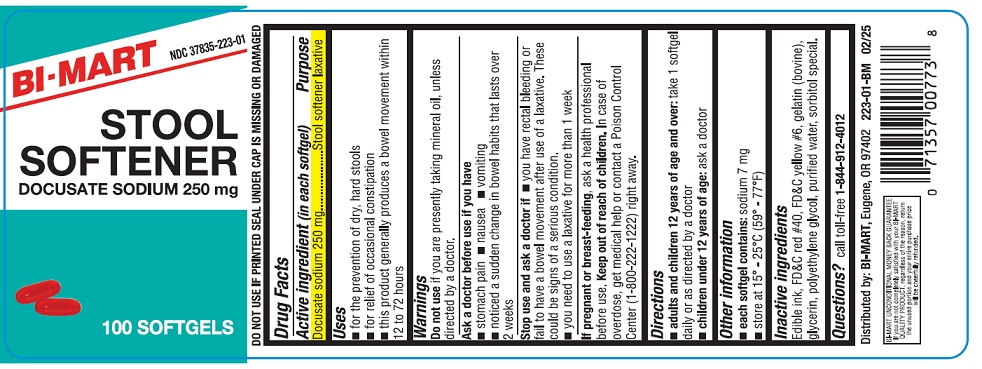 DRUG LABEL: STOOL SOFTENER
NDC: 37835-223 | Form: CAPSULE, LIQUID FILLED
Manufacturer: Bi-Mart
Category: otc | Type: HUMAN OTC DRUG LABEL
Date: 20250301

ACTIVE INGREDIENTS: DOCUSATE SODIUM 250 mg/1 1
INACTIVE INGREDIENTS: FD&C YELLOW NO. 6; FD&C RED NO. 40; GLYCERIN; GELATIN TYPE B BOVINE (160 BLOOM); POLYETHYLENE GLYCOL, UNSPECIFIED; WATER; SORBITOL SOLUTION

ACTIVE INGREDIENT (IN EACH SOFTGEL)

Docusate sodium 100 mg

PURPOSE

Stool softener laxative

USES

- for the prevention of dry, hard stools
- for relief of occasional constipation
- this product generally produces a bowel movement within 12 to 72 hours

WARNINGS

Do not useif you are presently taking mineral oil, unless directed by a doctor.

Ask a doctor before use if you have

- stomach pain
- nausea
- vomiting
- noticed a sudden change in bowel habits that lasts over 2 weeks

Stop use and ask a doctor if

- you have rectal bleeding or fail to have a bowel movement after use of a laxative. These could be signs of a serious condition.
- you need to use a laxative for more than 1 week

If pregnant or breast-feeding,ask a health professional before use.

Keep out of reach of children.In case of overdose, get medical help or contact a Poison Control Center (1-800-222-1222) right away.

DIRECTIONS

- adults and children 12 years of age and over:take 1 softgel daily or as directed by a doctor
- children under 12 years of age:ask a doctor

OTHER INFORMATION

- each softgel contains:sodium 7 mg
- store at 15°- 25°C (59°- 77°F)

INACTIVE INGREDIENTS

Edible ink, FD&C red #40, FD&C yellow #6, gelatin (bovine), glycerin, polyethylene glycol, purified water, sorbitol special.

QUESTIONS?

call toll free 1-844-912-4012

Distributed by:

BI-MART

Eugene, OR 97402